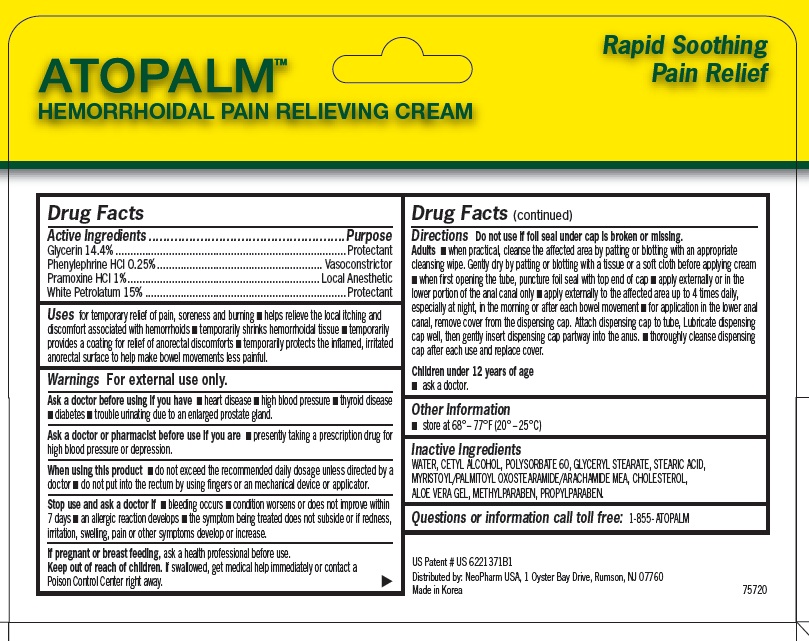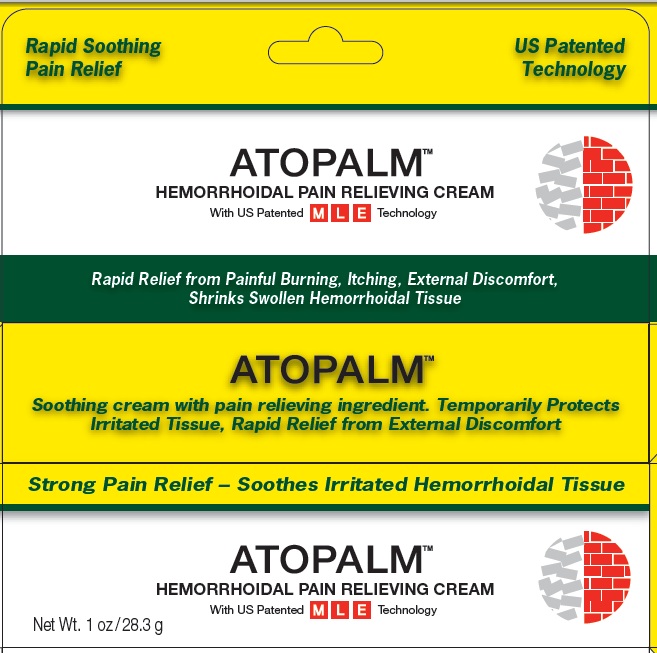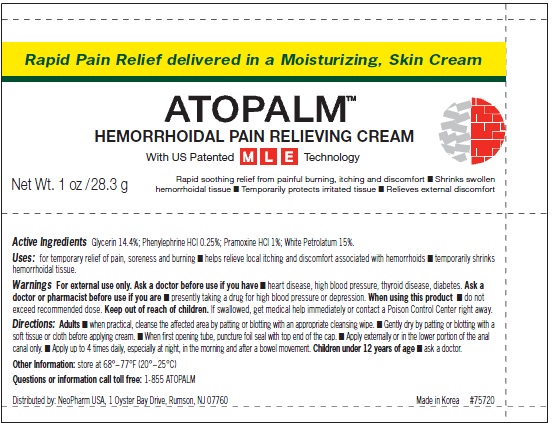 DRUG LABEL: ATOPALM Hemorrhoidal Pain Relieving
NDC: 51141-0220 | Form: CREAM
Manufacturer: NeoPharm USA
Category: otc | Type: HUMAN OTC DRUG LABEL
Date: 20120119

ACTIVE INGREDIENTS: GLYCERIN 14.4 g/100 g; PHENYLEPHRINE HYDROCHLORIDE 0.25 g/100 g; PRAMOXINE HYDROCHLORIDE 1.0 g/100 g; PETROLATUM 15 g/100 g
INACTIVE INGREDIENTS: WATER; CETYL ALCOHOL; POLYSORBATE 60; GLYCERYL MONOSTEARATE; STEARIC ACID; MYRISTOYL/PALMITOYL OXOSTEARAMIDE/ARACHAMIDE MEA; CHOLESTEROL; ALOE VERA LEAF; METHYLPARABEN; PROPYLPARABEN

ATOPALM Hemorrhoidal Pain Relieving Cream

Active Ingredient

Glycerin 14.4%
Phenylephrine HCl 0.25%
Pramoxine HCl 1%
White Petrolatum 15%

Purpose

Protectant
Vasoconstrictor
Local Anesthetic
Protectant

Uses

for temporary relief of pain, soreness and burning ■ helps relieve the local itching and discomfort associated with hemorrhoids ■ temporarily shrinks hemorrhoidal tissue ■ temporarily provides a coating for relief of anorectal discomforts ■ temporarily protects the inflamed, irritated anorectal surface to help make bowel movements less painful.

Warnings

For external use only.

Ask a doctor before using if you have

■ heart disease ■ high blood pressure ■ thyroid disease ■ diabetes ■ trouble urinating due to an enlarged prostate gland

Ask a doctor of pharmacist before use if you are

■ presently taking a prescription drug for high blood pressure or depression.

When using this product

■ do not exceed the recommended daily dosage unless directed by a doctor ■ do not put into the rectum by using fingers or an mechanical device or applicator.

Stop use and ask a doctor if

■ bleeding occurs ■ condition worsens or does not improve within 7 days ■ an allergic reaction develops ■ the symptom being treated does not subside or if redness, irritation, swelling, pain or other symptoms develop or increase.

If pregnant or breast feeding,

ask a health professional before use.

Keep out of reach of children.

If swallowed, get medical help immediately or contact a Poison Control Center right away.

Directions

Do not use if foil seal under cap is broken or missing.

Adults ■ when practical, cleanse the affected area by patting or blotting with an appropriate cleansing wipe. Gently dry by patting or blotting with a tissue or a soft cloth before applying cream ■ when first opening the tube, puncture foil seal with top end of cap ■ apply externally or in the lower portion of the anal canal only ■ apply externally to the affected area up to 4 times daily, especially at night, in the morning or after each bowel movement ■ for application in the lower anal canal, remove cover from the dispensing cap. Attach dispensing cap to tube, Lubricate dispensing
cap well, then gently insert dispensing cap partway into the anus. ■ thoroughly cleanse dispensing cap after each use and replace cover.

Children under 12 years of age
■ ask a doctor.

STORAGE AND HANDLING

■ store at 68° – 77°F (20° – 25°C)

Inactive Ingredients

WATER, CETYL ALCOHOL, POLYSORBATE 60, GLYCERYL STEARATE, STEARIC ACID, MYRISTOYL/PALMITOYL OXOSTEARAMIDE/ARACHAMIDE MEA, CHOLESTEROL, ALOE VERA GEL, METHYLPARABEN, PROPYLPARABEN.

Questions or information call toll free

1-855- ATOPALM

Product Labeling

Rapid Soothing Pain Relief

US Patented Technology

ATOPALM
HEMORRHOIDAL PAIN RELIEVING CREAM
With US Patented MLE Technology

Rapid Relief from Painful Burning, Itching, External Discomfort, Shrinks Swollen Hemorrhoidal Tissue

Soothing cream with pain relieving ingredient. Temporarily Protects Irritated Tissue, Rapid Relief from External Discomfort

Strong Pain Relief – Soothes Irritated Hemorrhoidal Tissue

Net Wt. 1 oz /28.3 g

US Patent # US 6221371B1
Distributed by: NeoPharm USA, 1 Oyster Bay Drive, Rumson, NJ 07760
Made in Korea